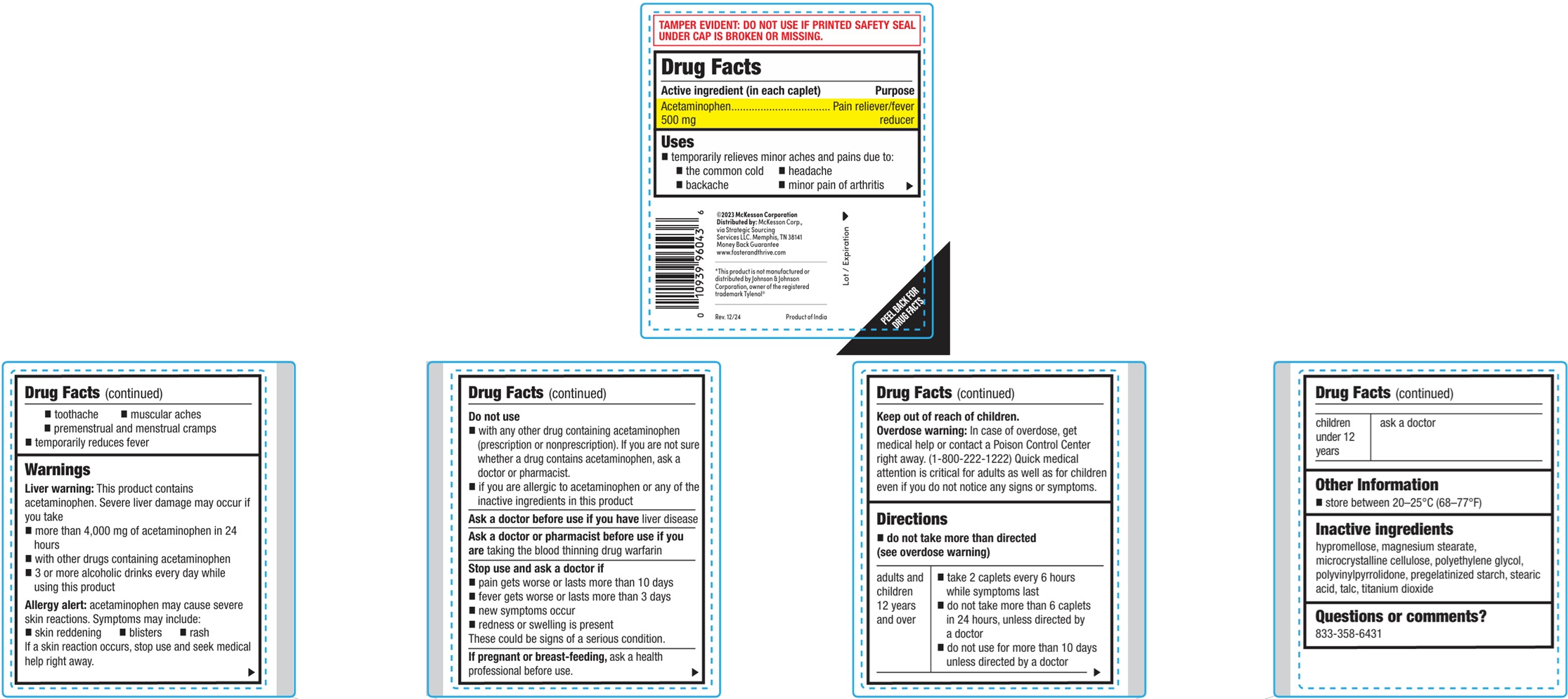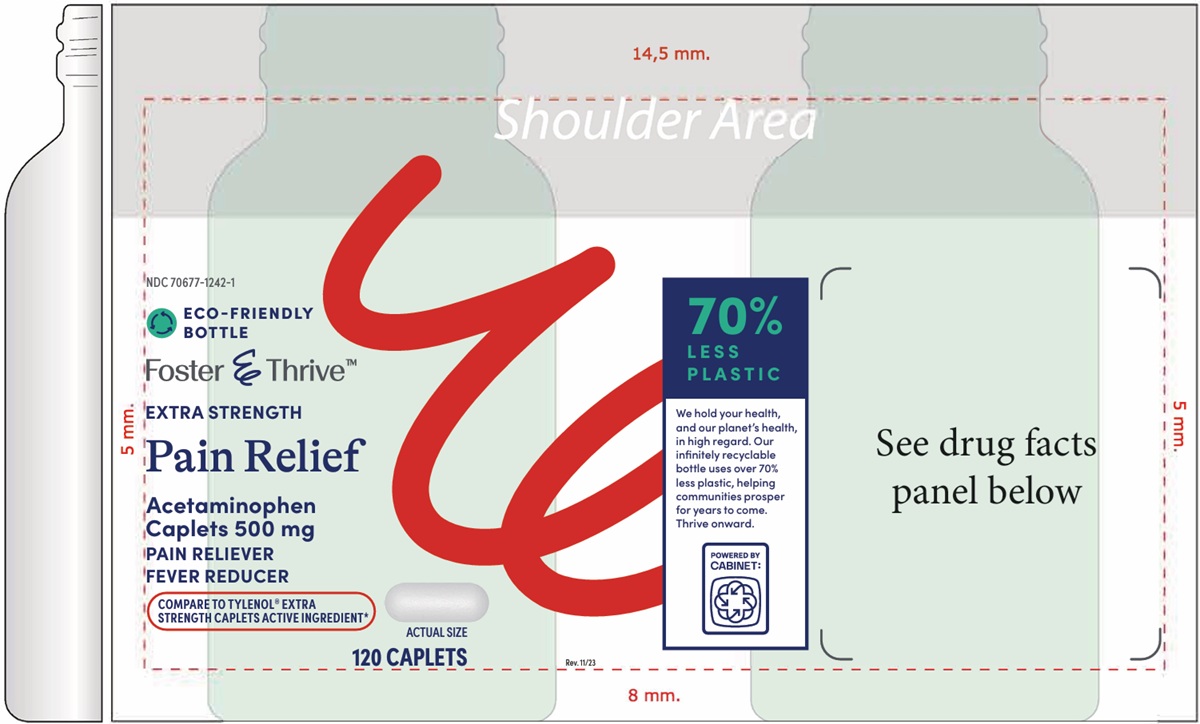 DRUG LABEL: EXTRA STRENGTH PAIN RELEIF
NDC: 70677-1242 | Form: TABLET, FILM COATED
Manufacturer: Strategic Sourcing Services, LLC
Category: otc | Type: HUMAN OTC DRUG LABEL
Date: 20260129

ACTIVE INGREDIENTS: ACETAMINOPHEN 500 mg/1 1
INACTIVE INGREDIENTS: HYPROMELLOSES; MAGNESIUM STEARATE; MICROCRYSTALLINE CELLULOSE; POLYETHYLENE GLYCOL, UNSPECIFIED; POVIDONE; STARCH, CORN; STEARIC ACID; TALC; TITANIUM DIOXIDE

EXTRA STRENGTH PAIN RELIEF

Inactive ingredients

Hypromellose, magnesium stearate, microcrystalline cellulose, polyethylene glycol, polyvinylpyrrolidone, pregelatinized starch, stearic acid, talc, titanium dioxide